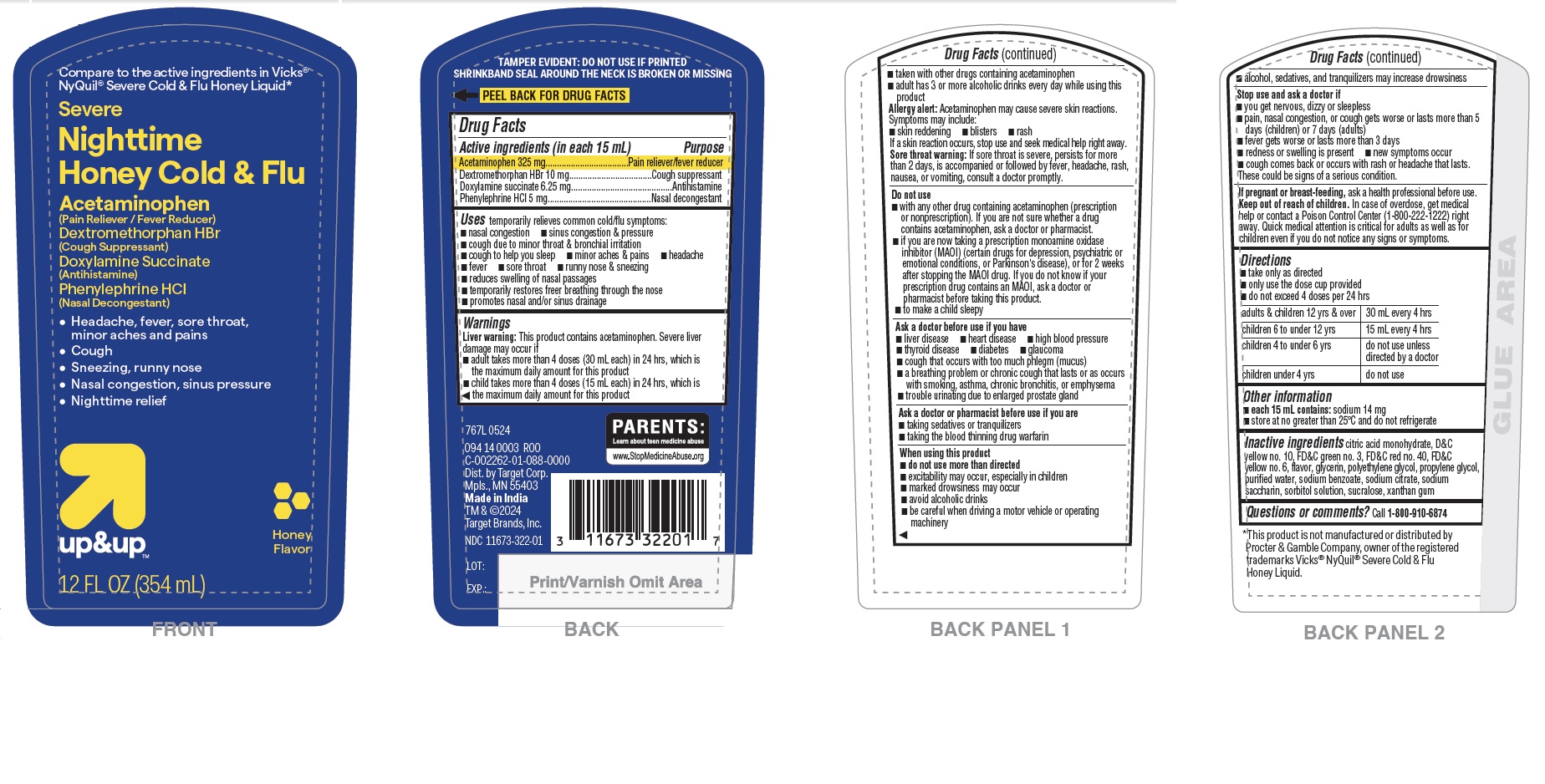 DRUG LABEL: Nighttime Severe Honey
NDC: 11673-322 | Form: LIQUID
Manufacturer: TARGET CORPORATION
Category: otc | Type: HUMAN OTC DRUG LABEL
Date: 20240629

ACTIVE INGREDIENTS: DOXYLAMINE SUCCINATE 6.25 mg/15 mL; ACETAMINOPHEN 325 mg/15 mL; DEXTROMETHORPHAN HYDROBROMIDE 10 mg/15 mL; PHENYLEPHRINE HYDROCHLORIDE 5 mg/15 mL
INACTIVE INGREDIENTS: D&C YELLOW NO. 10; SODIUM CITRATE; POLYETHYLENE GLYCOL, UNSPECIFIED; WATER; FD&C YELLOW NO. 6; SODIUM BENZOATE; FD&C GREEN NO. 3; SORBITOL SOLUTION; XANTHAN GUM; FD&C RED NO. 40; GLYCERIN; PROPYLENE GLYCOL; SUCRALOSE; CITRIC ACID MONOHYDRATE; SACCHARIN SODIUM

Target Nighttime Severe Cold & Flu Liquid - Honey

Active ingredients (in each 15 mL)

Acetaminophen 325 mg

Dextromethorphan HBr 10 mg

Doxylamine succinate 6.25 mg

Phenylephrine HCl 5 mg

Purpose

Pain reliever/fever reducer

Cough suppressant

Antihistamine

Nasal decongestant

INDICATIONS AND USAGE

Uses temporarily relieves common cold/flu symptoms:

- nasal congestion
- sinus congestion & pressure
- cough due to minor throat & bronchial irritation
- cough to help you sleep
- minor aches & pains
- headache
- fever
- sore throat
- runny nose & sneezing
- reduces swelling of nasal passages
- temporarily restores freer breathing through the nose
- promotes nasal and/or sinus drainage

WARNINGS

Liver warning: This product contains acetaminophen. Severe liver damage may occur if

- adult takes more than 4 doses (30 mL each) in 24 hrs, which is the maximum daily amount for this product
- child takes more than 4 doses (15 mL each) in 24 hrs, which is the maximum daily amount for this product
- taken with other drugs containing acetaminophen
- adult has 3 or more alcoholic drinks every day while using this product

Allergy alert: Acetaminophen may cause severe skin reactions. Symptoms may include:

- skin reddening
- blisters
- rash

If a skin reaction occurs, stop use and seek medical help right away.

Sore throat warning: If sore throat is severe, persists for more than 2 days, is accompanied or followed by fever, headache, rash, nausea, or vomiting, consult a doctor promptly.

Do not use

- with any other drug containing acetaminophen (prescription or nonprescription). If you are not sure whether a drug contains acetaminophen, ask a doctor or pharmacist.
- if you are now taking a prescription monoamine oxidase inhibitor (MAOI) (certain drugs for depression, psychiatric or emotional conditions, or Parkinson's disease), or for 2 weeks after stopping the MAOI drug. If you do not know if your prescription drug contains an MAOI, ask a doctor or pharmacist before taking this product.
- to make a child sleepy

Ask a doctor before use if you have

- liver disease
- heart disease
- high blood pressure
- thyroid disease
- diabetes
- glaucoma
- cough that occurs with too much phlegm (mucus)
- a breathing problem or chronic cough that lasts or as occurs with smoking, asthma, chronic bronchitis, or emphysema
- trouble urinating due to enlarged prostate gland

Ask a doctor or pharmacist before use if you are

- taking sedatives or tranquilizers
- taking the blood thinning drug warfarin.

When using this product

- do not use more than directed
- excitability may occur, especially in children
- marked drowsiness may occur
- avoid alcoholic drinks
- be careful when driving a motor vehicle or operating machinery
- alcohol, sedatives, and tranquilizers may increase drowsiness

Stop use and ask a doctor if

- you get nervous, dizzy or sleepless
- pain, nasal congestion, or cough gets worse or lasts more than 5 days (children) or 7 days (adults)
- fever gets worse or lasts more than 3 days
- redness or swelling is present
- new symptoms occur
- cough comes back or occurs with rash or headache that lasts

These could be signs of a serious condition.

PREGNANCY OR BREAST FEEDING

If pregnant or breast-feeding, ask a health professional before use.

Keep out of reach of children. In case of overdose, get medical help or contact a Poison Control Center (1-800-222-1222) right away. Quick medical attention is critical for adults as well as for children even if you do not notice any signs or symptoms.

Directions

- take only as directed
- only use the dose cup provided
- do not exceed 4 doses per 24 hrs

adults & children 12 yrs & over | 30 mL every 4 hrs
children 6 to under 12 yrs | 15 mL every 4 hrs
children 4 to under 6 yrs | do not use unless directed by a doctor
children under 4 yrs | do not use

Other information

- each 15 mL contains: sodium 14 mg
- store at no greater than 25℃ and do not refrigerate

INACTIVE INGREDIENT

Inactive ingredients citric acid monohydrate, D&C yellow no. 10, FD&C green no. 3, FD&C red no. 40, FD&C yellow no. 6, flavor, glycerin, polyethylene glycol, propylene glycol, purified water, sodium benzoate, sodium citrate, sodium saccharin, sorbitol solution, sucralose, xanthan gum

Questions or comments? Call 1-800-910-6874